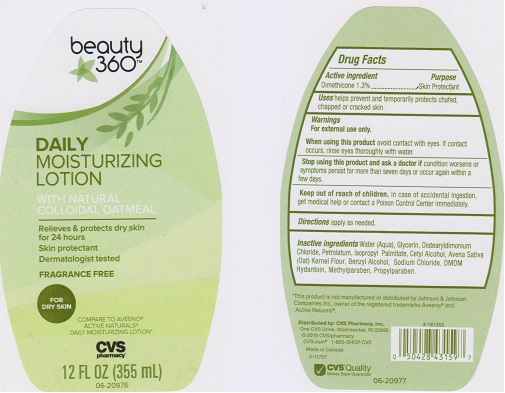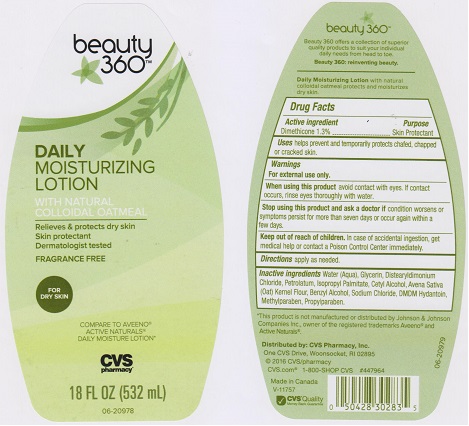 DRUG LABEL: CVS daily moisturizing 
NDC: 59779-323 | Form: LOTION
Manufacturer: CVS Pharmacy
Category: otc | Type: HUMAN OTC DRUG LABEL
Date: 20160309

ACTIVE INGREDIENTS: DIMETHICONE 13 mg/1 mL
INACTIVE INGREDIENTS: OATMEAL; BENZYL ALCOHOL; CETYL ALCOHOL; DISTEARYLDIMONIUM CHLORIDE; GLYCERIN; ISOPROPYL PALMITATE; PETROLATUM; SODIUM CHLORIDE; METHYLPARABEN; PROPYLPARABEN; DMDM HYDANTOIN; WATER

Drug Facts Box - Back Label

Active Ingredient

Dimethicone 1.3%

Purpose

Skin Protectant

Directions

Apply as needed

Warnings

For external use only.

When using this product

avoid contact with eyes. If contact occurs, rinse with water

Stop using this product and ask a doctor if

condition worsens or symptoms persist for more than seven days or occur again within a few days.

Keep out of reach of children.

In case of accidental ingestion, get medical help or contact a Poison Control Center immediately.

Uses

helps prevent and temporarily protects chafed, chapped or cracked skin.

Inactive ingredients

Water (Aqua), Glycerin, Distearyldimonium Chloride, Petrolatum, Isopropyl palmitate, Cetyl Alcohol, Avena Sativa (Oat) Kernel Flour, Benzyl Alcohol, Sodium Chloride, DMDM Hydantoin, Methylparaben, Propylparaben.